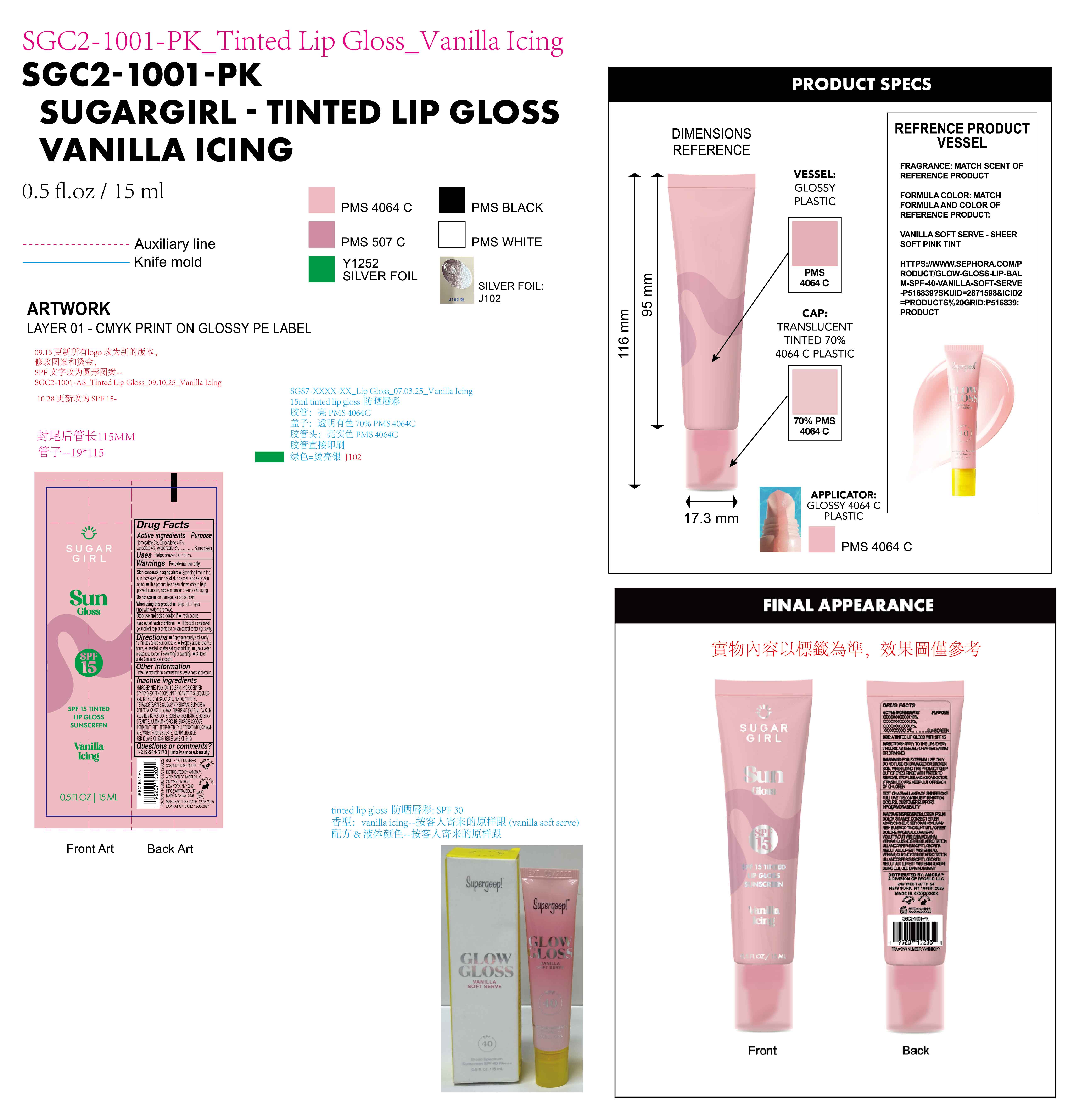 DRUG LABEL: Sugargirl sun gloss SPF15  tinted lip gloss Sunscreen Vanilla Icing
NDC: 85161-151 | Form: GEL
Manufacturer: Longway Technology(Guangzhou)Co.,Ltd.
Category: otc | Type: HUMAN OTC DRUG LABEL
Date: 20251204

ACTIVE INGREDIENTS: OCTOCRYLENE 0.045 g/1 mL; ETHYLHEXYL SALICYLATE 0.04 g/1 mL; AVOBENZONE 0.03 g/1 mL; HOMOSALATE 0.05 g/1 mL
INACTIVE INGREDIENTS: POLYMETHYLSILSESQUIOXANE (11 MICRONS); HYDROGENATED POLY(C6-14 OLEFIN; 4 CST); BUTYLOCTYL SALICYLATE; CALCIUM ALUMINUM BOROSILICATE; SORBITAN ISOSTEARATE; SUCROSE COCOATE; CI 16035; PENTAERYTHRITYL TETRA-DI-T-BUTYL HYDROXYHYDROCINNAMATE; SILICA; PENTAERYTHRITYL TETRAISOSTEARATE; STYRENE/ISOPRENE COPOLYMER (28:72; 210000 MW); CI 45410; SODIUM CHLORIDE; SYNTHETIC WAX (540 MW); EUPHORBIA CERIFERA (CANDELILLA) WAX; FRAGRANCE 13576; SORBITAN STEARATE; WATER; ALUMINUM HYDROXIDE; SODIUM SULFATE

ACTIVE INGREDIENT

Homosalate 5%, Octocrylene 4.5%, Octisalate 4% , Avobenzone 3%

Keep out of reach of children.

If product is swallowed get medical help or contact a poison control center right away.

QUESTIONS

1-212-244-5170 info@amora.beauty

PURPOSE

Sunscreen

OTHER SAFETY INFORMATION

Protect the product in this container from excessive heat and direct sun.

DOSAGE AND ADMINISTRATION

Apply generously and evenly15 minutes before sun exposure.

Reapply at least every 2hours, as needed, or after eating or drinking.

Use a water resistant sunscreen if swimming or sweating.

Children under 6 months: ask a doctor.

Warnings

For external use only.
Skin cancer/skin aging alert.

Spending time in the sun increases your risk of skin cancer and early skin aging.

This product has been shown only to help prevent sunburn, not skin cancer or early skin aging.

Do not use on damaged or broken skin.

When using this product . keep out of eyes. rinse with water to remove.

Stop use and ask a doctor if rash occurs.

Keep out of reach of children. lf product is swallowed get medical help or contact a poison control center right away

INDICATIONS AND USAGE

Helps prevent sunburn.

INACTIVE INGREDIENT

HYDROGENATED POLY(C6-14 OLEFIN),HYDROGENATED STYRENE/ISOPRENE COPOLYMER,POLYMETHYLSILSESQUIOXANE,BUTYLOCTYL SALICYLATE,PENTAERYTHRITYL TETRAISOSTEARATE,SILICA,SYNTHETIC WAX,EUPHORBIA CERIFERA (CANDELILLA) WAX,FRAGRANCE (PARFUM),CALCIUM ALUMINUM BOROSILICATE,SORBITAN ISOSTEARATE,SORBITAN STEARATE,ALUMINUM HYDROXIDE,SUCROSE COCOATE,PENTAERYTHRITYL TETRA-DI-T-BUTYL HYDROXYHYDROCINNAMATE,WATER,SODIUM SULFATE,SODIUM CHLORIDE, RED 40 LAKE(CI 16035), RED 28 LAKE(CI 45410)